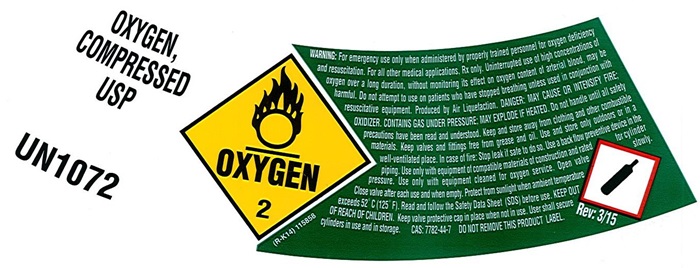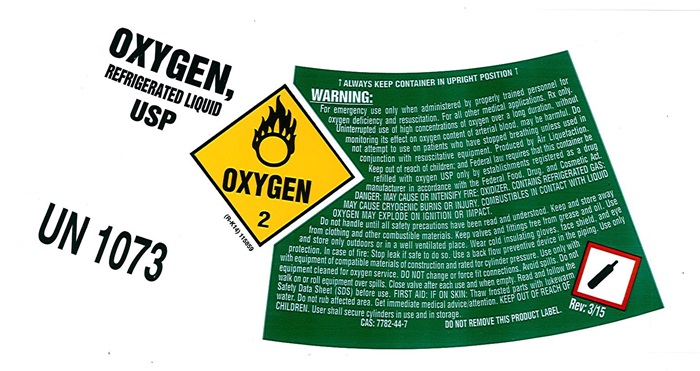 DRUG LABEL: OXYGEN
NDC: 48599-345 | Form: GAS
Manufacturer: Airweld, Inc.
Category: prescription | Type: HUMAN PRESCRIPTION DRUG LABEL
Date: 20241008

ACTIVE INGREDIENTS: OXYGEN 99 L/100 L

Oxygen

OXYGEN COMPRESSED LABEL

OXYGEN COMPRESSED USP

UN 1072

OXYGEN 2

(R-K14) 115858

WARNING: For emergency use only when administered by properly trained personnel for oxygen deficiency and resuscitation. For all other medical applications, Rx only. Uninterrupted use of high concentrations of oxygen over a long duration without monitoring its effect on oxygen content of arterial blood may be harmful. Do not attempt to use on patients who have stopped breathing unless used in conjunction with resuscitative equipment. Produced by Air Liquefaction. DANGER: MAY CAUSE OR INTENSIFY FIRE; OXIDIZER. CONTAINS GAS UNDER PRESSURE; MAY EXPLODE IF HEATED. Do not handle until all safety precautions have been read and understood. Keep and store away from clothing and other combustible materials. Keep valves and fittings free from grease and oil. Use and store only outdoors or in a well-ventilated place. In case of fire: Stop leak if safe to do so. Use a backflow preventive device in the piping. Use only with equipment cleaned for oxygen service. Open valve slowly. Close valve after each use and when empty. Protect from sunlight when ambient temperature exceeds 52° C (125°F). Read and follow the Safety data Sheet (SDS) before use. KEEP OUT OF THE REACH OF CHILDREN. Keep valve protective cap in place when not in use. User shall secure cylinders in use and in storage. CAS: 7782-44-7 DO NOT REMOVE THIS PRODUCT LABEL Rev: 3/15

OXYGEN REFRIGERATED LABEL

OXYGEN,

REFRIGERATED LIQUID USP

OXYGEN 2

UN 1073

(R-K14)115859

↑ ALWAYS KEEP CONTAINER IN UPRIGHT POSITION ↑

WARNING:

For emergency use only when administered by properly trained personnel for oxygen deficiency and resuscitation. For all other medical applications, Rx only. Uninterrupted use of high concentrations of oxygen over a long duration without monitoring its effect on oxygen content of arterial blood may be harmful. Do not attempt to use on patients who have stopped breathing unless used in conjunction with resuscitative equipment. Produced by Air Liquefaction. Keep out of the reach of children: and Federal law requires that this container be refilled with oxygen USP only by establishments registered as a drug manufacture in accordance with the Federal Food, Drug, and Cosmetic Act. DANGER: MAY CAUSE OR INTENSIFY FIRE; OXIDIZER. CONTAINS REFRIGERATED GAS: MAY CAUSE CRYOGENIC BURNS OR INJURY. COMBUSTIBLES IN CONTACT WITH LIQUID OXYGEN MAY EXPLODE OR IGNITION ON IMPACT.

Do not handle until all safety precautions have been read and understood. Keep and store away from clothing and other combustible materials. Keep valves and fittings free from grease and oil. Use and store only outdoors or in a well ventilated place. Wear cold insulating gloves, face shield, and eye protection. In case of fire: Stop leak if safe to do so. Use a back flow preventive device in the piping. Use only with equipment of compatible materials of construction and rated for cylinder pressure. Use only with equipment cleaned for oxygen service. DO NOT change or force fit connections. Avoid spills. Do not walk on or roll equipment over spills. Close valve after each use and when empty. Read and follow the Safety Data Sheet (SDS) before use. FIRST AID: IF ON SKIN: Thaw frosted parts with lukewarm water. Do not rub affected area. Get immediate medical attention. KEEP OUT OF REACH OF CHILDREN. User shall secure cylinders in use and storage.

CAS: 7782-44-7 DO NOT REMOVE THIS PRODUCT LABEL Rev:3/15